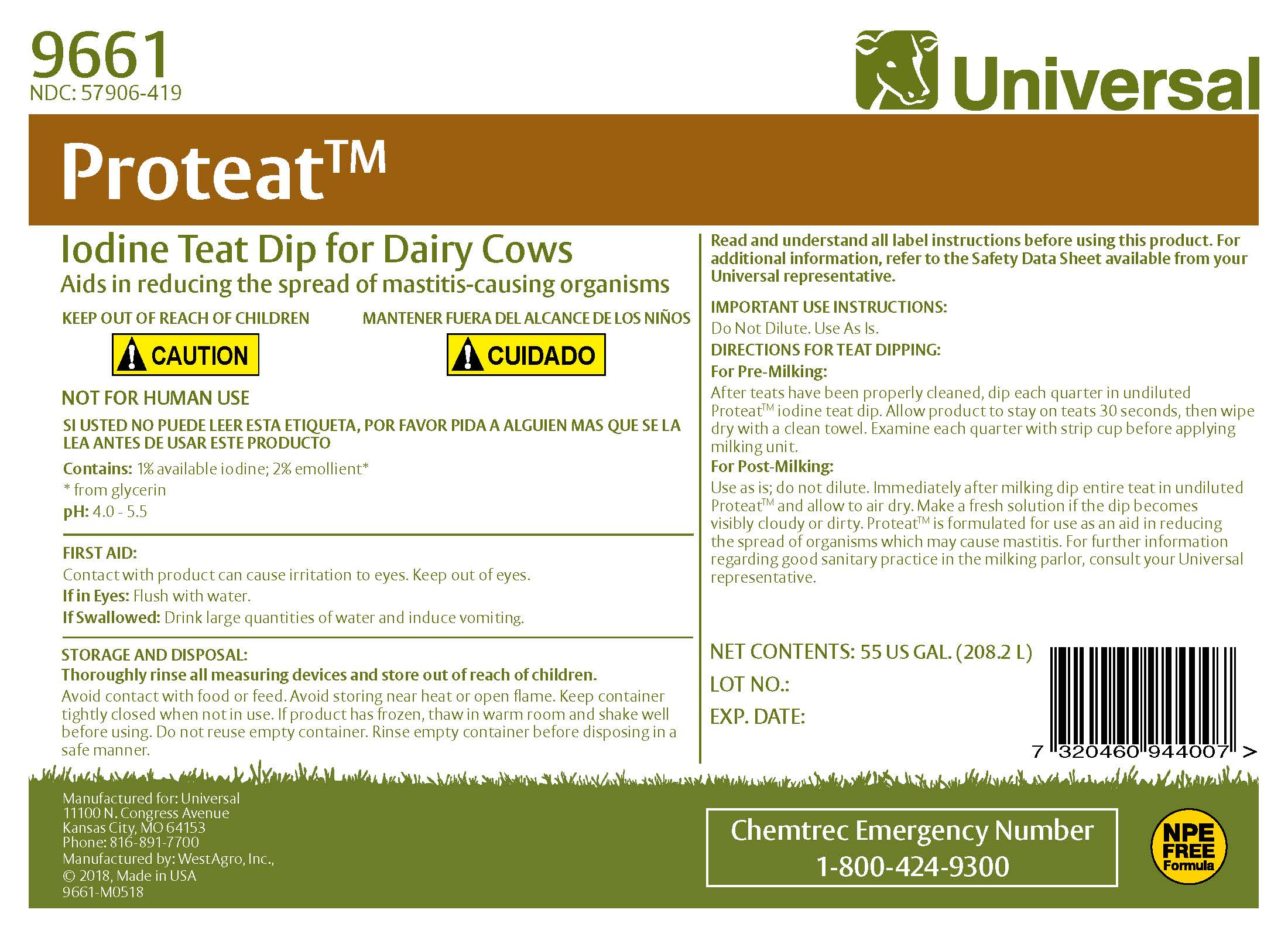 DRUG LABEL: Proteat
NDC: 57906-419 | Form: SOLUTION
Manufacturer: Universal
Category: animal | Type: OTC ANIMAL DRUG LABEL
Date: 20220120

ACTIVE INGREDIENTS: IODINE 10.2 g/1 L
INACTIVE INGREDIENTS: SODIUM HYDROXIDE; ANHYDROUS CITRIC ACID; GLYCERIN; XANTHAN GUM; POLOXAMER 335; SODIUM IODIDE; NONOXYNOL-12; WATER

Universal Proteat

INDICATIONS AND USAGE

Iodine Teat Dip for Cows

Aids in reducing the spread of mastitis-causing organisms

Important Use Instructions

DO NOT DILUTE. USE AS IS.

Read and understand all label instructions before using this product. For additonal information, refer to the Material Safety Data Sheet available from your Universal representative.

DOSAGE AND ADMINISTRATION

DIRECTIONS FOR TEAT DIPPING

FOR PRE-MILKING:

After teats have been properly cleaned, dip each quarter in undiluted PROTEAT iodine teat dip. Allow product to stay on teats 30 seconds, then wipe dry with a clean towel. Examine each quarter with strip cup before applying milking unit.

FOR POST-MILKING:

Use as is; do not dilute. Immediately after milking dip entire teat in undiluted PROTEAT and allow to air dry. Make a fresh solution if the dip becomes visibly cloudy or dirty. PROTEAT is formulated for use as an aid in reducing the spread of organisms which may cause mastitis. For further information regarding good sanitary practice in the milking parlor, consult your Universal representative.

FIRST AID

Contact with product can cause irritation to eyes. Keep out of eyes.

Eye Contact: Flush with water.

If Swallowed: Drink large quantities of water and induce vomiting.

STORAGE AND DISPOSAL:

THOROUGHLY RINSE ALL MEASURING DEVICES AND STORE OUT OF REACH OF CHILDREN. Avoid contact with food or feed. Avoid storing near heat or open flame. Keep container tightly closed when not in use. If product has frozen, thaw in warm room and shake well before using. Do not reuse empty container. Rinse empty container before disposing in a safe manner.

NOT FOR HUMAN USE

KEEP OUTOF REACH OF CHILDREN

! CAUTION

MANTENER FUERA DEL ALCANCE DE LOS NINOS

! CUIDADO

ACTIVE INGREDIENT

Contains: 1% available iodine

2% emollient*

* from glycerin

pH 4.0 - 5.5

Manufactured for: Universal
11100 N. Congress Avenue
Kansas City, MO 64153
Phone: 816-891-7700
Manufactured by: WestAgro, Inc.
©2018, Made in USA

Chemtrec Emergency Number

1-800-424-9300

Net Contents:

Lot No.:

Expiration Date: